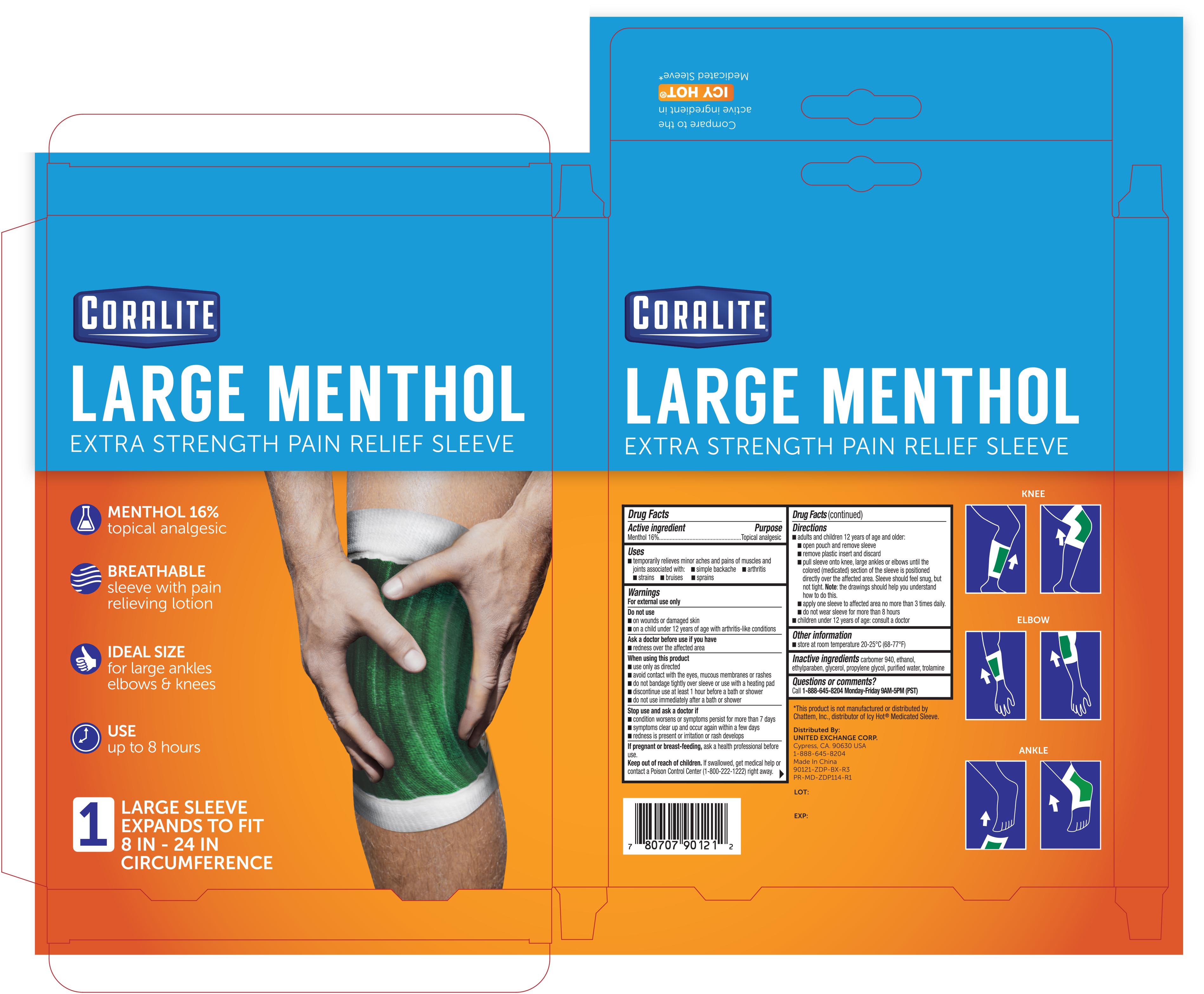 DRUG LABEL: Coralite Extra Strength Pain Relief Sleeve Knee
NDC: 65923-121 | Form: PATCH
Manufacturer: United Exchange Corp.
Category: otc | Type: HUMAN OTC DRUG LABEL
Date: 20251022

ACTIVE INGREDIENTS: MENTHOL 336 mg/1 1
INACTIVE INGREDIENTS: TROLAMINE; CARBOMER 940; ALCOHOL; GLYCERIN; PROPYLENE GLYCOL; WATER; ETHYLPARABEN

Coralite Large Menthol Pain Relief Sleeve 1ct 90121 ZDP

Active ingredient Purpose

Menthol 16.0%..................................................Topical Analgesic Patch

Uses

- temporarily relieves minor aches and pains of muscles and joints associated with:
- simple backache
- arthritis
- strains
- bruises
- sprains

Warnings

For external use only

Do not use

- on wounds or damaged skin
- on a child under 12 years of age with arthritis-like-conditions

Ask a doctor before use if you have

- redness over the affected area

When using this product

- use only as directed
- avoid contact with the eyes, mucous membranes or rashes
- do not bandage tightly over sleeve or use with a heating pad
- discontinue use at least 1 hour before a bath or shower
- do not use immediately after a bath or shower

Stop use and ask a doctor if

- condition worsens or symptoms persist for more than 7 days
- symptoms clear up and occur again within a few days
- redness is present or irritation or rash develops

PREGNANCY OR BREAST FEEDING

If pregnant or breast-feeding, ask a health professional before use

Keep out of reach of children. If swallowed, get medical help or contact a Poison Control Center (1-800-222-1222) right away

Directions

- adults and children 12 years of age and older:
- open pouch and remove sleeve
- remove plastic insert and discard
- pull sleeve onto knee, large ankles or elbows until the colored (medicated) section of the sleeve is positioned directly over the affected area. Sleeve should feel snug, but not tight. Note: the drawings should help you understand how to do this.
- apply one sleeve to affected area no more than 3 times daily
- do not wear sleeve for more than 8 hours
- children under 12 years of age: consult a doctor

Other information

- store at room temperature 20-25°C (68-77°F)

INACTIVE INGREDIENT

Inative ingredients

carbomer 940, ethanol, ethylparaben, glycerol, propylene glycol, purified water, trolamine

DOSAGE AND ADMINISTRATION

Distributed by:

United Exchange Corp.

Cypress, CA 90630 USA

Made in China